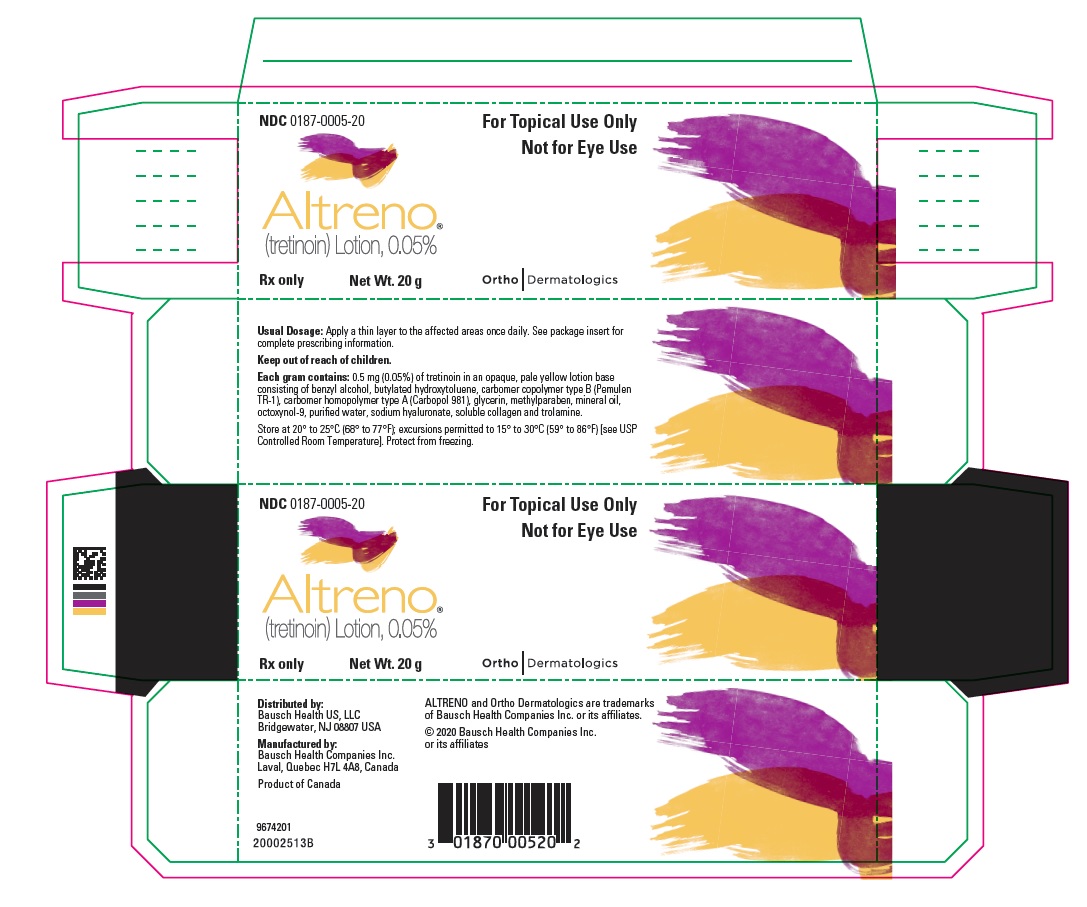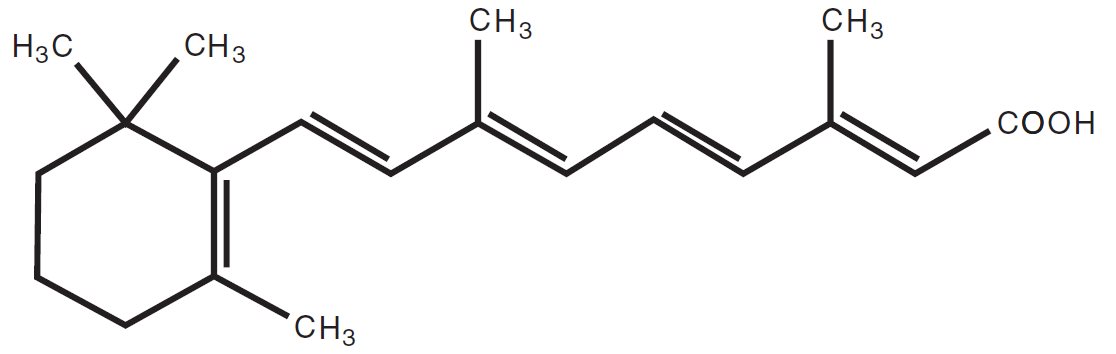 DRUG LABEL: Altreno
NDC: 0187-0005 | Form: LOTION
Manufacturer: Bausch Health US, LLC
Category: prescription | Type: HUMAN PRESCRIPTION DRUG LABEL
Date: 20200302

ACTIVE INGREDIENTS: TRETINOIN 0.5 mg/1 g
INACTIVE INGREDIENTS: BENZYL ALCOHOL; BUTYLATED HYDROXYTOLUENE; CARBOMER COPOLYMER TYPE B (ALLYL PENTAERYTHRITOL CROSSLINKED); CARBOMER HOMOPOLYMER TYPE A (ALLYL PENTAERYTHRITOL CROSSLINKED); GLYCERIN; METHYLPARABEN; MINERAL OIL; OCTOXYNOL-9; WATER; HYALURONATE SODIUM; TROLAMINE; MARINE COLLAGEN, SOLUBLE

HIGHLIGHTS OF PRESCRIBING INFORMATION

These highlights do not include all the information needed to use ALTRENO safely and effectively. See full prescribing information for ALTRENO.
ALTRENO® (tretinoin) lotion, for topical use
Initial U.S. Approval: 1973

1 INDICATIONS AND USAGE

ALTRENO is a retinoid indicated for the topical treatment of acne vulgaris in patients 9 years of age and older. (1)

2 DOSAGE AND ADMINISTRATION

- Apply a thin layer of ALTRENO to affected areas once daily. Avoid eyes, mouth, paranasal creases, and mucous membranes. (2)
- Not for ophthalmic, oral, or intravaginal use. (2)

3 DOSAGE FORMS AND STRENGTHS

Lotion, 0.05% (3)

Each gram of ALTRENO contains 0.5 mg (0.05%) tretinoin. (3)

4 CONTRAINDICATIONS

None. (4)

5 WARNINGS AND PRECAUTIONS

- Skin Irritation: Dryness, pain, erythema, irritation and exfoliation may occur with use of ALTRENO. (5.1)
- Ultraviolet Light and Environmental Exposure: Minimize exposure to sunlight and sunlamps. Use sunscreen and protective clothing when sun exposure cannot be avoided. (5.2)
- Fish Allergies: Use ALTRENO with caution if allergic to fish due to potential for allergenicity to fish protein. Advise patients to contact their healthcare provider if they develop pruritus or urticaria. (5.3)

6 ADVERSE REACTIONS

- The most common adverse reactions occurring in ≥1% of subjects and greater than vehicle were dryness, pain, erythema, irritation and exfoliation (all at the application site). (6.1)

To report SUSPECTED ADVERSE REACTIONS, contact Bausch Health US, LLC at 1-800-321-4576 or FDA at 1-800-FDA-1088 or www.fda.gov/medwatch.

FULL PRESCRIBING INFORMATION

1 INDICATIONS AND USAGE

ALTRENO® (tretinoin) lotion, 0.05% is indicated for the topical treatment of acne vulgaris in patients 9 years of age and older.

2 DOSAGE AND ADMINISTRATION

Apply a thin layer of ALTRENO to the affected areas once daily. Avoid the eyes, mouth, paranasal creases, and mucous membranes.

ALTRENO is for topical use only. Not for ophthalmic, oral, or intravaginal use.

3 DOSAGE FORMS AND STRENGTHS

Lotion, 0.05%

Each gram of ALTRENO contains 0.5 mg (0.05%) tretinoin in an opaque, pale yellow topical lotion.

4 CONTRAINDICATIONS

None.

5 WARNINGS AND PRECAUTIONS

5.1 Skin Irritation

Patients using ALTRENO may experience application site dryness, pain, erythema, irritation, and exfoliation. Depending upon the severity of these adverse reactions, instruct patients to use a moisturizer, reduce the frequency of the application of ALTRENO, or discontinue use. Avoid application of ALTRENO to eczematous or sunburned skin.

5.2 Ultraviolet Light and Environmental Exposure

Minimize unprotected exposure to ultraviolet light including sunlight and sunlamps during the use of ALTRENO. Warn patients who normally experience high levels of sun exposure and those with inherent sensitivity to sun to exercise caution. Use sunscreen products and protective clothing over treated areas when sun exposure cannot be avoided.

5.3 Fish Allergies

ALTRENO contains soluble fish proteins. Use with caution in patients with known sensitivity or allergy to fish. Advise patients to contact their healthcare provider if they develop pruritus or urticaria.

6 ADVERSE REACTIONS

6.1 Clinical Trials Experience

Because clinical trials are conducted under widely varying conditions, adverse reaction rates observed in the clinical trials of a drug cannot be directly compared to rates in the clinical trials of another drug and may not reflect the rates observed in clinical practice.

In 2 randomized, double-blind, vehicle-controlled trials, subjects age 9 years and older applied ALTRENO or vehicle once daily for 12 weeks. The majority of subjects were White (74%) and female (55%). Approximately 47% were Hispanic/Latino and 45% were younger than 18 years of age. Adverse reactions reported by ≥1% of subjects treated with ALTRENO and more frequently than vehicle are summarized in Table 1.

Table 1: Adverse Reactions Reported by ≥1% of Subjects Treated with ALTRENO and More Frequently than Vehicle
Adverse Reactions
n (%)
 | ALTRENO N=767 | Vehicle N=783
Application site dryness | 29 (4) | 1 (<1)
Application site pain [Application site pain defined as application site stinging, burning or pain.] | 25 (3) | 3 (<1)
Application site erythema | 12 (2) | 1 (<1)
Application site irritation | 7 (1) | 1 (<1)
Application site exfoliation | 6 (1) | 3 (<1)

Skin irritation was evaluated by active assessment of erythema, scaling, hypopigmentation, hyperpigmentation, itching, burning and stinging. The percentage of subjects who were assessed to have these signs and symptoms at any post baseline visit are summarized in Table 2.

Table 2: Application Site Tolerability Reactions at Any Post Baseline Visit
 | ALTRENO; N=760; Mild/Mod/Severe | Vehicle; N=782; Mild/Mod/Severe
Erythema | 51% | 44%
Scaling | 49% | 30%
Hypopigmentation | 12% | 10%
Hyperpigmentation | 35% | 35%
Itching | 35% | 28%
Burning | 30% | 14%
Stinging | 21% | 8%

8 USE IN SPECIFIC POPULATIONS

8.1 Pregnancy

Risk Summary

Available data from published observational studies of topical tretinoin in pregnant women have not established a drug-associated risk of major birth defects, miscarriage, or adverse maternal or fetal outcomes. There are no data on ALTRENO use in pregnant women.

The systemic levels following topical administration are lower than with administration of oral tretinoin; however, absorption of this product may result in fetal exposure. There are reports of major birth defects similar to those seen in infants exposed to oral retinoids, but these case reports do not establish a pattern or association with tretinoin-related embryopathy (see Data).

Animal reproduction studies have not been conducted with ALTRENO. Topical administration of tretinoin in a different formulation to pregnant rats during organogenesis was associated with malformations (craniofacial abnormalities [hydrocephaly], asymmetrical thyroids, variations in ossification, and increased supernumerary ribs) at doses up to 0.5 mg tretinoin/kg/day, approximately 2 times the maximum recommended human dose (MRHD) based on body surface area (BSA) comparison and assuming 100% absorption. Oral administration of tretinoin to pregnant cynomolgus monkeys during organogenesis was associated with malformations at 10 mg/kg/day (approximately 100 times the MRHD based on BSA comparison and assuming 100% absorption) (see Data).

The estimated background risk of major birth defects and miscarriage for the indicated population is unknown. All pregnancies have a background risk of major birth defects, loss, and other adverse outcomes. The background risk in the U.S. general population of major birth defects is 2 to 4% and of miscarriage is 15 to 20% of clinically recognized pregnancies.

Data

Human Data

While available studies cannot definitively establish the absence of risk, published data from multiple prospective controlled observational studies on the use of topical tretinoin products during pregnancy have not identified an association with topical tretinoin and major birth defects or miscarriage. The available studies have methodologic limitations, including small sample size and in some cases, lack of physical exam by an expert in birth defects. There are published case reports of infants exposed to topical tretinoin during the first trimester that describe major birth defects similar to those seen in infants exposed to oral retinoids; however, no pattern of malformations has been identified and no causal association has been established in these cases. The significance of these spontaneous reports in terms of risk to the fetus is not known.

Animal Data

Tretinoin in a 0.05% gel formulation was topically administered to pregnant rats during organogenesis at doses of 0.1, 0.3 and 1 g/kg/day (0.05, 0.15, 0.5 mg tretinoin/kg/day). Possible tretinoin malformations (craniofacial abnormalities [hydrocephaly], asymmetrical thyroids, variations in ossification, and increased supernumerary ribs) were observed at maternal doses of 0.5 mg tretinoin/kg/day (approximately 2 times the MRHD based on BSA comparison and assuming 100% absorption). These findings were not observed in control animals. Other maternal and reproductive parameters in tretinoin-treated animals were not different from control. For purposes of comparison of the animal exposure to human exposure, the MRHD is defined as 4 g of ALTRENO applied daily to a 60 kg person.

Other topical tretinoin embryofetal development studies have generated equivocal results. There is evidence for malformations (shortened or kinked tail) after topical administration of tretinoin to pregnant Wistar rats during organogenesis at doses greater than 1 mg/kg/day (approximately 5 times the MRHD based on BSA comparison and assuming 100% absorption). Anomalies (humerus: short 13%, bent 6%, os parietal incompletely ossified 14%) have also been reported when 10 mg/kg/day (approximately 50 times the MRHD based on BSA comparison and assuming 100% absorption) was topically applied to pregnant rats during organogenesis. Supernumerary ribs have been a consistent finding in rat fetuses when pregnant rats were treated topically or orally with retinoids.

Oral administration of tretinoin during organogenesis has been shown to induce malformations in rats, mice, rabbits, hamsters, and nonhuman primates. Fetal malformations were observed when tretinoin was orally administered to pregnant Wistar rats during organogenesis at doses greater than 1 mg/kg/day (approximately 5 times the MRHD based on BSA comparison). In the cynomolgus monkey, fetal malformations were reported when an oral dose of 10 mg/kg/day was administered to pregnant monkeys during organogenesis (approximately 100 times the MRHD based on BSA comparison). No fetal malformations were observed at an oral dose of 5 mg/kg/day (approximately 50 times the MRHD based on BSA comparison). Increased skeletal variations were observed at all doses in this study and dose-related increases in embryo lethality and abortion were reported in this study. Similar results have also been reported in pigtail macaques.

Oral tretinoin has been shown to be fetotoxic in rats when administered at doses 10 times the MRHD based on BSA comparison. Topical tretinoin has been shown to be fetotoxic in rabbits when administered at doses 4 times the MRHD based on BSA comparison.

8.2 Lactation

Risk Summary

There are no data on the presence of tretinoin or its metabolites in human milk, the effects on the breastfed infant, or the effects on milk production. It is not known whether topical administration of tretinoin could result in sufficient systemic absorption to produce detectable concentrations in human milk. The developmental and health benefits of breastfeeding should be considered along with the mother’s clinical need for ALTRENO and any potential adverse effects on the breastfed child from ALTRENO.

8.4 Pediatric Use

Safety and effectiveness of ALTRENO for the topical treatment of acne vulgaris have been established in pediatric patients age 9 years to less than 17 years based on evidence from two multicenter, randomized, double-blind, parallel-group, vehicle-controlled, 12-week trials and an open-label pharmacokinetic study. A total of 318 pediatric subjects aged 9 to less than 17 years received ALTRENO in the clinical studies [see Clinical Pharmacology (12.3) and Clinical Studies (14)].

The safety and effectiveness of ALTRENO in pediatric patients below the age of 9 years have not been established.

8.5 Geriatric Use

Clinical trials of ALTRENO did not include any subjects age 65 years and older to determine whether they respond differently from younger subjects.

11 DESCRIPTION

ALTRENO (tretinoin) lotion is an opaque, pale yellow lotion containing 0.05% tretinoin by weight for topical administration.

Chemically, tretinoin is all-trans-retinoic acid, also known as (all-E)-3,7-dimethyl-9-(2,6,6-trimethyl-1-cyclohexen-1-yl)-2,4,6,8-nonatetraenoic acid. It is a member of the retinoid class of compounds and a metabolite of vitamin A. Tretinoin has the following chemical structure:

Molecular Formula: C20H28O2 Molecular Weight: 300.44

Each gram of ALTRENO contains 0.5 mg (0.05%) of tretinoin in an opaque, pale yellow lotion base consisting of benzyl alcohol, butylated hydroxytoluene, carbomer copolymer type B (Pemulen TR-1), carbomer homopolymer type A (Carbopol 981), glycerin, methylparaben, mineral oil, octoxynol-9, purified water, sodium hyaluronate, soluble collagen and trolamine.

12 CLINICAL PHARMACOLOGY

12.1 Mechanism of Action

Tretinoin is a metabolite of vitamin A that binds with high affinity to specific retinoic acid receptors located in both the cytosol and nucleus.

Tretinoin activates three members of the retinoic acid (RAR) nuclear receptors (RARα, RARβ, and RARγ) which act to modify gene expression, subsequent protein synthesis, and epithelial cell growth and differentiation. It has not been established whether the clinical effects of tretinoin are mediated through activation of retinoic acid receptors, other mechanisms, or both.

Although the exact mode of action of tretinoin in acne treatment is unknown, current evidence suggests that topical tretinoin decreases cohesiveness of follicular epithelial cells with decreased microcomedo formation. Additionally, tretinoin stimulates mitotic activity and increased turnover of follicular epithelial cells causing extrusion of the comedones.

12.2 Pharmacodynamics

The pharmacodynamics of ALTRENO in the treatment of acne vulgaris are unknown.

12.3 Pharmacokinetics

Plasma concentrations of tretinoin and its major metabolites (isotretinoin and 4-oxo-isotretinoin) were evaluated in 20 subjects in an open-label, randomized, pharmacokinetic study. Subjects aged 10 years to less than 17 years old with acne vulgaris applied approximately 3.5 g of ALTRENO to the skin of the entire face (excluding eyes and lips), neck, upper chest, upper back and shoulders once daily for 14 days. Single-dose pharmacokinetic (PK) characteristics were determined from samples drawn on Days 1 and 2 of dosing and steady-state PK characteristics were determined from samples drawn on Days 14 and 15 under maximal use conditions. The mean baseline corrected Cmax and AUC0-t of tretinoin and its metabolites after once daily application of ALTRENO for 14 days are shown below:

Compound | Mean (±SD) Cmax (ng/mL) | Mean (±SD) AUC0-t (ng*h/mL)
Tretinoin | 0.33 (0.33) | 6.46 (5.15)
Isotretinoin | 0.49 (0.66) | 9.30 (9.95)
4-oxo-isotretinoin | 0.57 (0.82) | 14.51 (18.28)

The mean concentrations of tretinoin and its metabolites (isotretinoin and 4‑oxo‑isotretinoin) remain relatively stable and unchanged over the 24‑hour period after both the Day 1 dose and the Day 14 dose. Systemic concentrations of tretinoin appear to be at or near steady state by Day 14. Mean accumulation ratios of the baseline corrected AUC between Day 14 and Day 1 were 1.5, 4.5 and 7.3 for tretinoin, isotretinoin, and 4-oxo-isotretinoin, respectively.

13 NONCLINICAL TOXICOLOGY

13.1 Carcinogenesis, Mutagenesis, Impairment of Fertility

A 2-year dermal mouse carcinogenicity study was conducted with topical administration of 0.005%, 0.025% and 0.05% of a tretinoin gel formulation. Although no drug-related tumors were observed in surviving animals, the irritating nature of the drug product precluded daily dosing, confounding data interpretation and reducing the biological significance of these results.

Studies in hairless albino mice with a different formulation suggest that concurrent exposure to tretinoin may enhance the tumorigenic potential of carcinogenic doses of UVB and UVA light from a solar simulator. This effect was confirmed in a later study in pigmented mice, and dark pigmentation did not overcome the enhancement of photocarcinogenesis by 0.05% tretinoin. Although the significance of these studies to humans is not clear, patients should minimize exposure to sunlight or artificial ultraviolet irradiation sources.

The genotoxic potential of tretinoin was evaluated in an in vitro bacterial reversion test, an in vitro chromosomal aberration assay in human lymphocytes and an in vivo rat micronucleus assay. All tests were negative.

In dermal fertility studies of another tretinoin formulation in rats, slight (not statistically significant) decreases in sperm count and motility were seen at 0.5 mg/kg/day (approximately 2 times the MRHD based on BSA comparison and assuming 100% absorption), and slight (not statistically significant) increases in the number and percent of nonviable embryos in females treated with 0.25 mg/kg/day and above (approximately the MRHD based on BSA comparison and assuming 100% absorption) were observed.

14 CLINICAL STUDIES

The safety and efficacy of once daily use of ALTRENO for the treatment of acne vulgaris were assessed in two multicenter, randomized, double-blind clinical trials enrolling 1640 subjects age 9 years and older with acne vulgaris. Enrolled subjects had a score of moderate (3) or severe (4) on the Evaluator’s Global Severity Score (EGSS), 20 to 40 inflammatory lesions (papules, pustules, and nodules), 20 to 100 non-inflammatory lesions (open and closed comedones) and two or fewer facial nodules. The coprimary efficacy endpoints of success on the EGSS, absolute change in noninflammatory lesion count, and absolute change in inflammatory lesion count were assessed at Week 12. Success on the EGSS was defined as at least a 2-grade improvement from Baseline and an EGSS score of clear (0) or almost clear (1). Table 3 lists the efficacy results for trials 1 (NCT02491060) and 2 (NCT02535871).

Table 3: Efficacy Results at Week 12
Trial 1 | ALTRENO N=406 | Vehicle N=414
EGSS
Clear or Almost Clear and | 16.5% | 6.9%
2-Grade Reduction from Baseline
Non-Inflammatory Facial Lesions
Mean Absolute Reduction | 17.8 | 10.6
Mean Percent Reduction | 47.5% | 27.3%
Inflammatory Facial Lesions
Mean Absolute Reduction | 13.1 | 10.2
Mean Percent Reduction | 50.9% | 40.4%
Trial 2 | ALTRENO N=413 | Vehicle N=407
EGSS
Clear or Almost Clear and; 2-Grade Reduction from Baseline | 19.8% | 12.5%
Non-Inflammatory Facial Lesions
Mean Absolute Reduction | 21.9 | 13.9
Mean Percent Reduction | 45.6% | 31.9%
Inflammatory Facial Lesions
Mean Absolute Reduction | 13.9 | 10.7
Mean Percent Reduction | 53.4% | 41.5%

16 HOW SUPPLIED/STORAGE AND HANDLING

ALTRENO (tretinoin) lotion, 0.05% is an opaque, pale yellow topical lotion and available as:

- 45 g tube (NDC 0187-0005-45)
- 20 g tube (NDC 0187-0005-20)
- 50 g pump (NDC 0187-0005-50)

Storage and Handling Conditions

Store at 20° to 25°C (68° to 77°F); excursions permitted to 15° to 30°C (59° to 86°F) [see USP Controlled Room Temperature]. Protect from freezing.

Store pump upright.

17 PATIENT COUNSELING INFORMATION

Advise the patient to read the FDA-approved patient labeling (Patient Information).

- Warn patients of the potential for skin irritation during treatment.
- Advise patients to minimize exposure to sunlight and sunlamps; recommend the use of sunscreen products and protective apparel (e.g., hat) when sun exposure cannot be avoided.

Distributed by:
Bausch Health US, LLC
Bridgewater, NJ 08807 USA

Manufactured by:
Bausch Health Companies Inc.
Laval, Quebec H7L 4A8, Canada

ALTRENO is a trademark of Bausch Health Companies Inc. or its affiliates.
© 2020 Bausch Health Companies Inc. or its affiliates
9650303

Patient Package Insert

PATIENT INFORMATION
ALTRENO® (al-TREN-oh)
(tretinoin) lotion, 0.05%
for topical use

Important information: ALTRENO is for use on skin only. Do not use ALTRENO in your eyes, mouth, the corners of your nose, or vagina.

What is ALTRENO?

ALTRENO is a prescription medicine used on the skin (topical) to treat people with acne. Acne is a condition in which the skin has blackheads, whiteheads, and other pimples.

It is not known if ALTRENO is safe and effective in children under 9 years of age.

Before using ALTRENO, tell your healthcare provider about all your medical conditions, including if you:

- are allergic to fish. ALTRENO contains fish proteins. Tell your healthcare provider if you get hives or itching while using ALTRENO.
- have eczema or any other skin problems.
- have a sunburn.
- are pregnant or plan to become pregnant. It is not known if ALTRENO will harm your unborn baby.
- are breastfeeding or plan to breastfeed. It is not known if ALTRENO passes into your breast milk.

Tell your healthcare provider about all the medicines you take, including prescription and over-the-counter medicines, vitamins, and herbal supplements. Know the medicines you take. Keep a list of them to show your healthcare provider and pharmacist when you get a new medicine.

How should I use ALTRENO?

- Use ALTRENO exactly as your healthcare provider tells you to use it.
- Apply a thin layer of ALTRENO to cover the affected areas 1 time each day.

Applying ALTRENO:

- ALTRENO comes in a tube and a pump. If you have been prescribed the:

Tube: Squeeze the lotion from the tube onto a fingertip. Apply a thin layer to cover the affected areas, as prescribed by your doctor. Spread ALTRENO evenly over the affected areas.

Pump: Fully depress the pump to dispense ALTRENO onto a fingertip. Apply a thin layer to cover the affected areas, as prescribed by your doctor. Spread ALTRENO evenly over the affected areas.

- Wash your hands after applying ALTRENO.

What should I avoid while using ALTRENO?

- You should avoid sunlamps, tanning beds, and ultraviolet light during treatment with ALTRENO.
- Minimize exposure to sunlight.
- If you have to be in the sunlight or are sensitive to sunlight, use a sunscreen with an SPF (sun protection factor) of 15 or more and wear protective clothing and a wide-brimmed hat to cover the treated areas.

What are the possible side effects of ALTRENO?

ALTRENO may cause serious side effects, including:

Skin irritation. ALTRENO may cause irritation including skin dryness, pain, redness, excessive flaking or peeling. If you develop these symptoms, your healthcare provider may tell you to use a moisturizer, decrease the number of times you apply ALTRENO, or completely stop treatment with ALTRENO. Avoid applying ALTRENO to skin that is affected by eczema or sunburned skin.

These are not all the possible side effects of ALTRENO.

Call your doctor for medical advice about side effects. You may report side effects to FDA at 1-800-FDA-1088.

How should I store ALTRENO?

- Store ALTRENO at room temperature between 68° to 77°F (20° to 25°C).
- Do not freeze.
- Store ALTRENO pump upright.

Keep ALTRENO and all medicines out of the reach of children.

General information about the safe and effective use of ALTRENO

Medicines are sometimes prescribed for purposes other than those listed in a Patient Information leaflet. Do not use ALTRENO for a condition for which it was not prescribed. Do not give ALTRENO to other people, even if they have the same symptoms that you have. It may harm them. You can ask your pharmacist or healthcare provider for information about ALTRENO that is written for health professionals.

What are the ingredients in ALTRENO?

Active ingredient: tretinoin

Inactive ingredients: benzyl alcohol, butylated hydroxytoluene, carbomer copolymer type B (Pemulen TR-1), carbomer homopolymer type A (Carbopol 981), glycerin, methylparaben, mineral oil, octoxynol-9, purified water, sodium hyaluronate, soluble collagen and trolamine.

Distributed by:
Bausch Health US, LLC, Bridgewater, NJ 08807 USA

Manufactured by:
Bausch Health Companies Inc., Laval, Quebec H7L 4A8, Canada

For more information, call 1-800-321-4576.

ALTRENO is a trademark of Bausch Health Companies Inc. or its affiliates.

© 2020 Bausch Health Companies Inc. or its affiliates

This Patient Information has been approved by the U.S. Food and Drug Administration.

9650303

Revised: 03/2020

PACKAGE/LABEL PRINCIPAL DISPLAY PANEL – Carton 20 g

NDC 0187-0005-20

For Topical Use Only
Not for Eye Use

ALTRENO®
(tretinoin) Lotion, 0.05%

Rx only

Net Wt. 20 g

Ortho Dermatologics